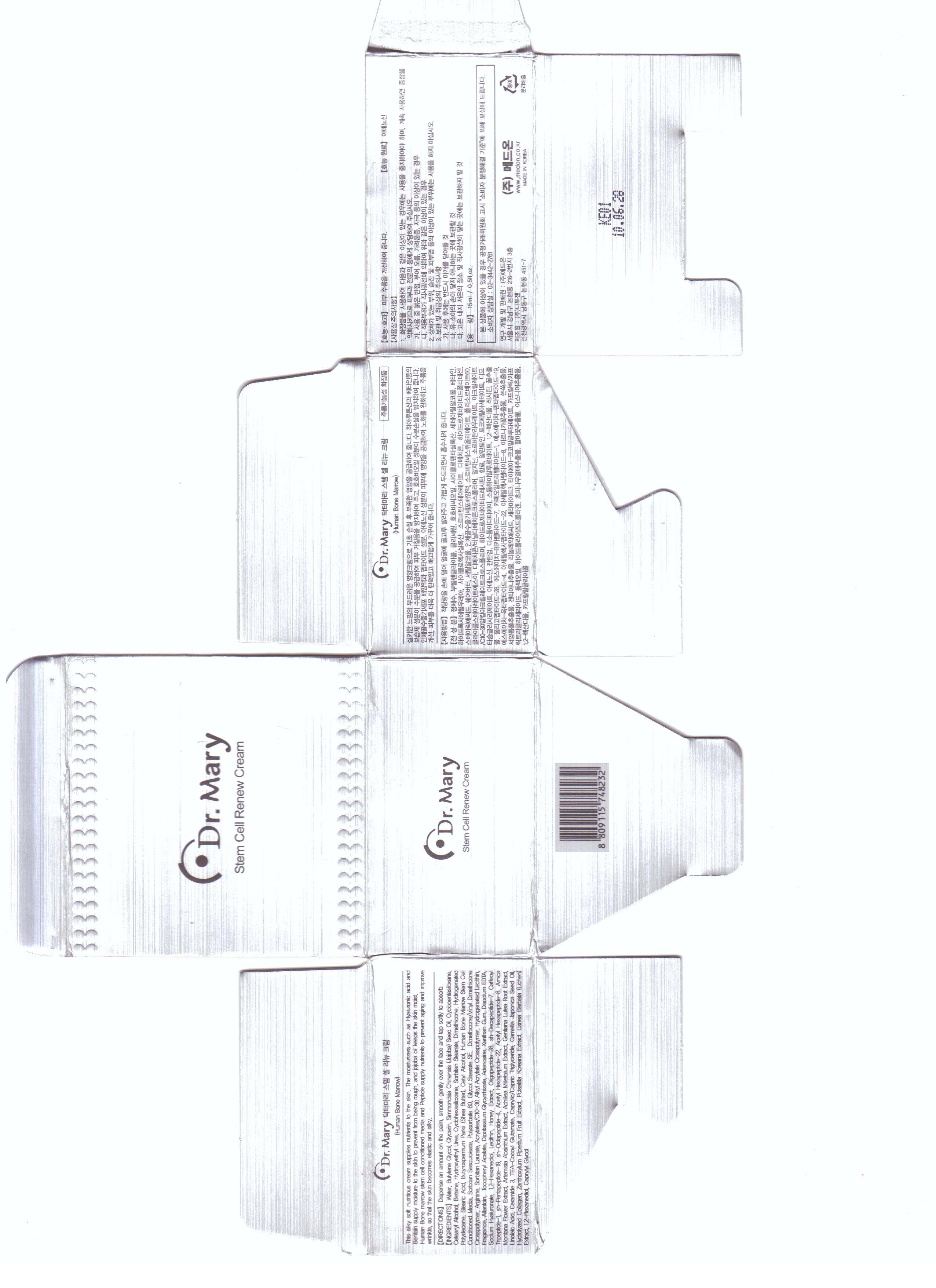 DRUG LABEL: Stem Cell Renew
NDC: 76071-1001 | Form: CREAM
Manufacturer: Medon Co., Ltd
Category: otc | Type: HUMAN OTC DRUG LABEL
Date: 20110406

ACTIVE INGREDIENTS: ADENOSINE 0.04 mL/1 mL
INACTIVE INGREDIENTS: PALMITOYL OLIGOPEPTIDE; PREZATIDE COPPER ACETATE; PENTIGETIDE; ACETYL HEXAPEPTIDE-3; WATER; BUTYLENE GLYCOL; GLYCERIN; BETAINE; SORBITAN; DIMETHICONE; STEARIC ACID; SHEA BUTTER; CETYL ALCOHOL; SORBITAN SESQUIOLEATE; POLYSORBATE 60; GLYCOL STEARATE; ARGININE; SORBITAN MONOLAURATE; HYDROGENATED SOYBEAN LECITHIN; ALLANTOIN; .ALPHA.-TOCOPHEROL ACETATE, D-; GLYCYRRHIZINATE DIPOTASSIUM; XANTHAN GUM; EDETATE DISODIUM; HYALURONATE SODIUM; HONEY; ARTEMISIA ABROTANUM FLOWERING TOP; ACHILLEA MILLEFOLIUM; GENTIANA LUTEA ROOT; LINOLEIC ACID; CERAMIDE 3; CAMELLIA JAPONICA FLOWER; USNEA BARBATA; CAPRYLYL GLYCOL

Drug Facts

active ingredient: adenosine

inactive ingredient: water, butylene glycol, glycerin, simmondsia, chinensis seed oil, cyclopentasiloxane, cetearyl alcohol, betaine, hydroxyethyl urea, cyclohexasiloxane, sorbitan stearate, dimethicone, hydrogenated polydecene, stearic acid, butyrospemum, shea butter, cetyl alcohol, human bone marrow stem cell conditioned media, sorbitan sesquioleate, polysorbate 60, glycol stearate SE, dimethicone/vinyl dimethicone crosspolymer, arginine, sorbitan laurate, acrylates/C10-30 alkyl acrylate crosspolymer, hydrogenated lecithin, fragrance, allantoin, tocopheryl acetate, dipotassium glycyrrhizate, adenosine, xanthan gum, disodium EDTA, sodium hyaluronate, 1,2-hexanediol, lecithin, honey extract, oligopeptide-28, sh-decapeptide-7, caffeoyl tripeptide-1, sh-pentapeptide-19, sh-octapeptide-4, acetyl hexapeptide-22, acetyl hexapeptide-8, amica montana flower etract, artemisia absinthium extract, achillea millefolium extract, gentiana lutea root extract, linoleic acid, ceramide 3, tea-cocoyl glutamate, caprylic/capric triglyceride, camellia japonica seed oil, hydrolyzed collagen, zanthoxylum piperitum fruit extract, pulsatilla koreana extract, usnea barbata extract, 1,2-hexanediol, caprylyl glycol

PURPOSE

anti aging and wrinkle, supplying nutrients

keep out of reach of the children

INDICATIONS AND USAGE

- cleansing the skin
- dispense an amount on the palm
- smooth gently over the face and tap softly to absorb

- do not use when you feel itching
- do not swallow
- clean the skin before use

DOSAGE AND ADMINISTRATION

for external use only